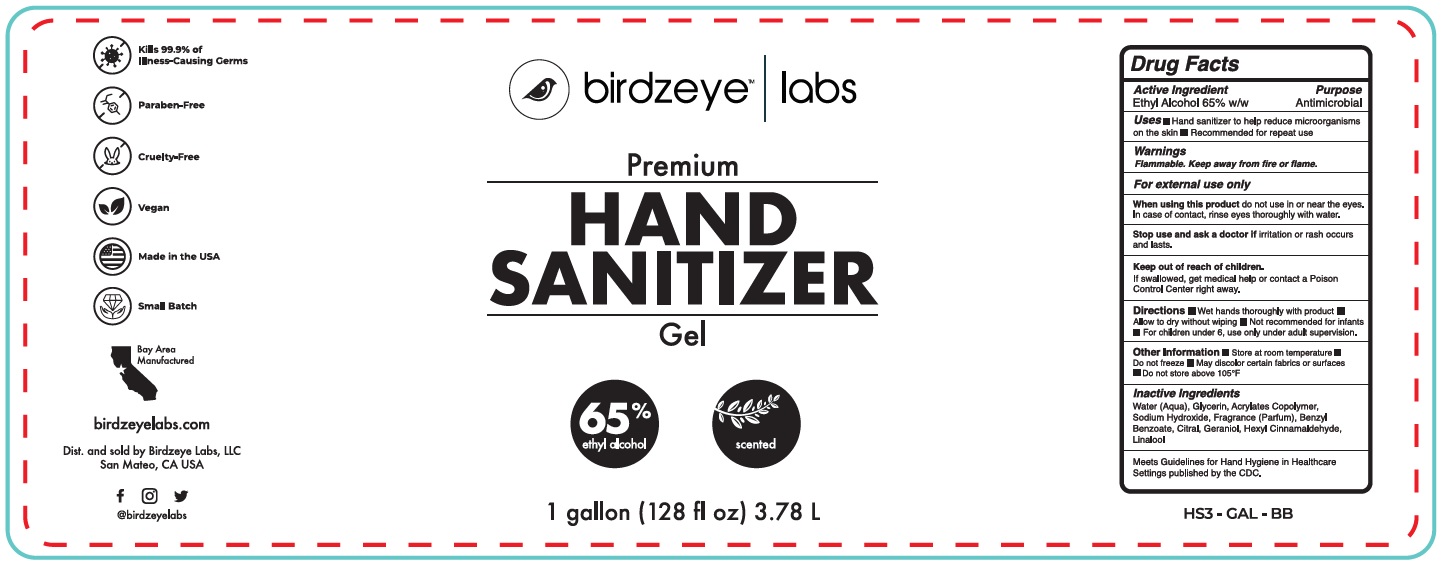 DRUG LABEL: Hand Sanitizer
NDC: 62742-4191 | Form: GEL
Manufacturer: Allure Labs Inc
Category: otc | Type: HUMAN OTC DRUG LABEL
Date: 20201125

ACTIVE INGREDIENTS: ALCOHOL 65 mL/100 mL
INACTIVE INGREDIENTS: .ALPHA.-HEXYLCINNAMALDEHYDE; BENZYL BENZOATE; CITRAL; GERANIOL; LINALOOL, (+/-)-; SODIUM HYDROXIDE; GLYCERIN; ACRYLATES CROSSPOLYMER-6; WATER

DRUG FACTS

Active Ingredient(s)

Ethyl Alcohol 65% w/w.

Purpose

Antimicrobial

Use

- Hand Sanitizer to help reduce microorganisms on the skin.
- Recommended for repeat use.

Warnings

For external use only. Flammable. Keep away from fire or flame

When using this product do not use in or near the eyes. In case of contact, rise eyes thouroughly with water.

Stop use and ask a doctor if irritation or rash occurs and lasts.

Keep out of reach of children. If swallowed, get medical help or contact a Poison Control Center right away.

Directions

- Wet hands thoroughly with product
- Allow to dry without wiping
- Not recommended for infants
- For children under 6, use only under adult supervision

Other information

- Store at room temperature
- Do not freeze
- May discolor certain fabrics or surfaces
- Do not store above 105 ºF

Inactive ingredients

Water(aqua), Glycerin, Acrylates Copolymer, Sodium Hydroxide, Fragrance (parfum), Benzyl Benzoate, Citral, Geraniol, Hexyl Cinnamaldehyde, linalool

Package Label - Principal Display Panel

Birdzeyelabs.com

Dist. and sold by Birdzeye Labs, LLC

San Mateo, CA USA